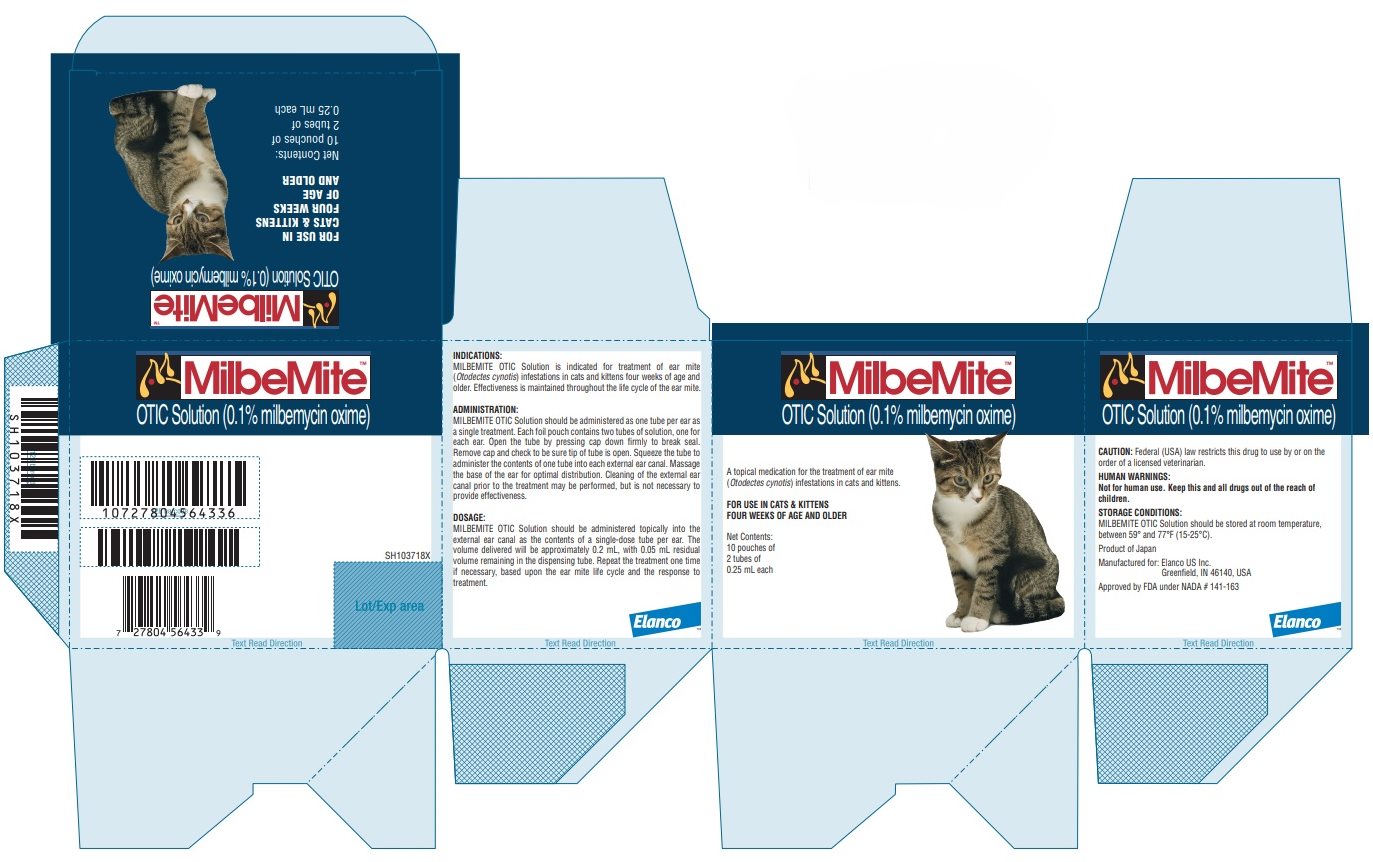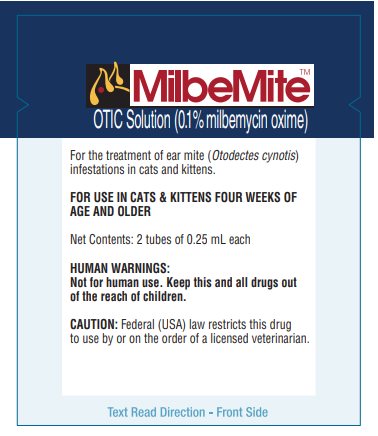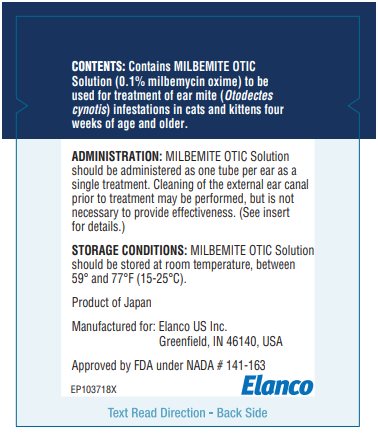 DRUG LABEL: Milbemite
NDC: 58198-8602 | Form: SOLUTION
Manufacturer: Elanco US Inc.
Category: animal | Type: PRESCRIPTION ANIMAL DRUG LABEL
Date: 20231213

ACTIVE INGREDIENTS: Milbemycin oxime 1 mg/1 mL

MILBEMITE™ OTIC Solution

(0.1% milbemycin oxime)

Caution: U.S. Federal law restricts this drug to use by or on the order of a licensed veterinarian.

Description:

MILBEMITE OTIC Solution is available in plastic dispensing tubes. Each plastic tube contains 0.25 mL of MILBEMITE OTIC Solution as a 0.1% solution of milbemycin oxime. Milbemycin oxime consists of the oxime derivatives of 5-didehydromilbemycins in the ratio of approximately 80% A4 (C32H45NO7, MW 555.71) and 20% A3 (C31H43NO7, MW 541.68).

Indications:

MILBEMITE OTIC Solution is indicated for treatment of ear mite (Otodectes cynotis) infestations in cats and kittens four weeks of age and older. Effectiveness is maintained throughout the life cycle of the ear mite.

Human Warnings:

Not for human use. Keep this and all drugs out of the reach of children.

Precautions:

The safe use of MILBEMITE OTIC Solution in cats used for breeding purposes, during pregnancy, or in lactating queens, has not been evaluated.

Adverse Reactions:

No adverse reactions caused by MILBEMITE OTIC Solution have been reported in controlled effectiveness studies in adult cats and kittens (4 weeks of age).

Dosage:

MILBEMITE OTIC Solution should be administered topically into the external ear canal as the entire contents of a single-dose tube per ear. The volume delivered will be approximately 0.2 mL, with 0.05 mL residual volume remaining in dispensing tube. Repeat the treatment one time if necessary, based upon the ear mite life cycle and the response to treatment.

Administration:

MILBEMITE OTIC Solution should be administered as one tube per ear as a single treatment. Each foil pouch contains two tubes of solution, one for each ear. Open the tube by pressing cap down firmly to break seal. Remove cap and check to be sure tip of tube is open. Squeeze the tube to administer the contents of one tube into each external ear canal. Massage the base of the ear for optimal distribution. In clinical field trials, ears were not cleaned and many animals still had debris in their ears at the end of the study. Cleaning of the external ear canal prior to treatment may be performed, but is not necessary to provide effectiveness.

Effectiveness:

The clinical effectiveness of milbemycin oxime 0.1% solution was evaluated in a placebo-controlled clinical field trial of client-owned cats. Otodectes cynotis infestation was diagnosed by direct microscopic visualization of ear swab debris. Test or placebo treatment was administered to both ears of the cat following the pre-treatment examination. Cats’ ears were examined by ear swab microscopy at multiple intervals throughout the life cycle of the mite (up to day 30). Ninety-nine percent (99%) of the milbemycin oxime-treated group were ear mite negative at the microscopic exams.

Safety:

A study was conducted using otic doses of 0.1, 0.3 or 0.5% milbemycin oxime solutions administered once weekly for six applications in kittens that were 4 weeks of age at the initiation of the study. Otic doses of 0.1 and 0.3% did not produce adverse systemic or local effects. One kitten treated with 0.5% was lethargic 8 hours after the second treatment. The kitten was offered milk replacer and by 10 hours post-treatment it appeared normal. In this kitten, lethargy was not observed after subsequent treatments. A study was conducted to evaluate the safety of a 0.1% milbemycin oxime solution in adult cats. Topical doses at 1X, 3X or 5X the recommended dose applied in one ear did not produce adverse effects.

Storage Conditions:

MILBEMITE OTIC Solution should be stored at room temperature, between 59° and 77°F (15-25°C).

How Supplied:

MILBEMITE OTIC Solution is supplied in individual white polypropylene tubes, paired in a foil overlay pouch. The product is packaged in a box of 10 pouches of 2 tubes of 0.25 mL each.

Product of Japan

Manufactured for: Elanco US Inc.
Greenfield, IN 46140, USA

Approved by FDA under NADA # 141-163

Milbemite, Elanco and the diagonal bar logo are trademarks of Elanco or its affiliates.

© 2022 Elanco or its affiliates

Revision Date: May 2022

PA103718X

ElancoTM

Principal Display Panel - Carton Label

MilbeMite™

OTIC Solution (0.1% milbemycin oxime)

A topical medication for the treatment of ear mite
(Otodectes cynotis) infestations in cats and kittens.

FOR USE IN CATS & KITTENS
FOUR WEEKS OF AGE AND OLDER

Net Contents:
10 pouches of
2 tubes of
0.25 mL each

Principal Display Panel - Pouch Label

MilbeMite™

OTIC Solution (0.1% milbemycin oxime)

For the treatment of ear mite (Otodectes cynotis)
infestations in cats and kittens.

FOR USE IN CATS & KITTENS FOUR WEEKS OF
AGE AND OLDER

Net Contents: 2 tubes of 0.25 mL each

HUMAN WARNINGS:
Not for human use. Keep this and all drugs out
of the reach of children.

CAUTION: Federal (USA) law restricts this drug
to use by or on the order of a licensed veterinarian.